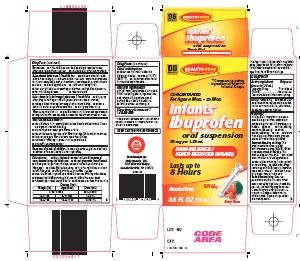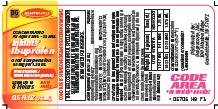 DRUG LABEL: Health Sense Infants Ibuprofen
NDC: 55910-057 | Form: SUSPENSION
Manufacturer: Dolgencorp Inc
Category: otc | Type: HUMAN OTC DRUG LABEL
Date: 20090522

ACTIVE INGREDIENTS: IBUPROFEN 50 mg/1.25 mL

Dollar General Health Sense Infants' Ibuprofen Oral Suspension, Berry Flavor Drug Facts

Active ingredient (in each 1.25 mL)

Ibuprofen 50 mg (NSAID)*

*nonsteroidal anti-inflammatory drug

Purpose

Pain reliever/fever reducer

Uses

temporarily:

- reduces fever
- relieves minor aches and pains due to the common cold, flu, sore throat, headaches and toothaches

Warnings

Allergy alert: Ibuprofen may cause a severe allergic reaction, especially in people allergic to aspirin. Symptoms may include:

- hives
- facial swelling
- asthma (wheezing)
- shock
- skin reddening
- rash
- blisters

If an allergic reaction occurs, stop use and seek medical help right away.

Stomach bleeding warning: This product contains a nonsteroidal anti-inflammatory drug (NSAID), which may cause stomach bleeding.

The chance is higher if the child:

- has had stomach ulcers or bleeding problems
- takes a blood thinning (anticoagulant) or steroid drug
- takes other drugs containing an NSAID [aspirin, ibuprofen, naproxen, or others]
- takes more or for a longer time than directed

Sore throat warning: Severe or persistent sore throat or sore throat accompanied by high fever, headache, nausea, and vomiting may be serious. Consult doctor promptly. Do not use more than 2 days or administer to children under 3 years of age unless directed by doctor.

Do not use

- if the child has ever had an allergic reaction to any other pain reliever/fever reducer
- right before or after heart surgery

Ask a doctor before use if the child has

- problems or serious side effects from taking pain relievers or fever reducers
- stomach problems that last or come back, such as heartburn, upset stomach, or stomach pain
- ulcers
- bleeding problems
- not been drinking fluids
- lost a lot of fluid due to vomiting or diarrhea
- high blood pressure
- heart or kidney disease
- taken a diuretic

Ask a doctor or pharmacist before use if the child is

- taking any other drug containing an NSAID (prescription or nonprescription)
- taking a blood thinning (anticoagulant) or steroid drug
- under a doctor’s care for any serious condition
- taking any other drug

When using this product

- give with food or milk if stomach upset occurs
- long term continuous use may increase the risk of heart attack or stroke

Stop use and ask a doctor if

- the child feels faint, vomits blood, or has bloody or black stools. These are signs of stomach bleeding.
- stomach pain or upset gets worse or lasts
- the child does not get any relief within first day (24 hours) of treatment
- fever or pain gets worse or lasts more than 3 days
- redness or swelling is present in the painful area
- any new symptoms appear

Keep out of reach of children.

In case of overdose, get medical help or contact a Poison Control Center right away.

Directions

- this product does not contain directions or complete warnings for adult use
- do not give more than directed
- do not give longer than 10 days, unless directed by a doctor (see Warnings)
- shake well before using
- find the right dose on chart below. If possible, use weight to dose; otherwise use age.
- measure with dosing device provided. Do not use with any other device.
- dispense liquid slowly into the child’s mouth, toward the inner cheek
- if needed, repeat dose every 6-8 hours
- do not use more than 4 times a day

Dosing Chart

Weight (lb) | Age (mos) | Dose (mL)
under 6 mos |  | ask a doctor
12-17 lbs | 6-11 mos | 1.25 mL
18-23 lbs | 12-23 mos | 1.875 mL

Other information

- do not use if printed neckband is broken or missing
- store at 20-25°C (68-77°F)
- see bottom of box for lot number and expiration date

Inactive ingredients

artificial flavor, butylparaben, citric acid, FD&C red #40, glycerin, hypromellose, polysorbate 80, propylene glycol, purified water, sodium benzoate, sorbitol, sucrose, xanthan gum

Questions or comments?

1-888-309-9030

Principal Display Panel

Compare to active ingredient of Motrin® Infants' Drops

Concentrated

For Ages 6 mos.-23 mos.

Infants' Ibuprofen Oral Suspension

50 mg per 1.25 mL

Pain Reliever/Fever Reducer (NSAID)

Lasts up to 8 hours

Alcohol Free

Use Only With Enclosed Syringe

Berry Flavor

Product Carton
Product Label